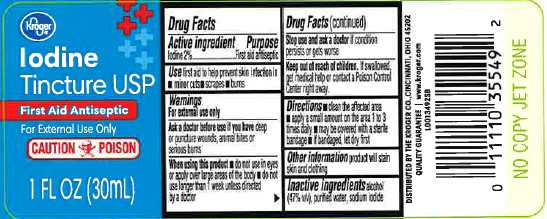 DRUG LABEL: Iodine Tincture
NDC: 30142-088 | Form: SOLUTION/ DROPS
Manufacturer: The Kroger Co.
Category: otc | Type: HUMAN OTC DRUG LABEL
Date: 20260227

ACTIVE INGREDIENTS: IODINE 20 mg/1 mL
INACTIVE INGREDIENTS: ALCOHOL; WATER; SODIUM IODIDE

Kroger 088.000/088AA
Iodine Tincture

Active ingredient

Iodine 2%

Purpose

First aid antiseptic

Use

First aid to help prevent skin infection in

- minor cuts
- scrapes
- burns

Warnings

For external use only

Ask a doctor before use

If you have deep or puncture wounds, animal bites or serious burns

when using this product

- do not use in eyes or apply over large areas of the body
- do not use longer than 1 week unless directed by a doctor

Stop use and ask a doctor

If condition persists or gets worse

Keep out of reach of children.

If swallowed, get medical help or contact a Poison Control Center right away.

Directions

- clean the affected area
- apply a small amount on the area 1 to 3 times daily
- may be covered with a sterile bandage
- if bandaged, let dry first

Inactive ingredients

alcohol (47% v/v), purified water, sodium iodide

Other information

Product will stain skin and clothing

ADVERSE REACTION

DISTRIBUTED BY THE KROGER CO., CINCINNATI, OHIO 45202

QUALITY GUARANTEE

www.kroger.com

principal display panel

KROGER®

IODINE TINCTURE USP

FIRST AID ANTISEPTIC

FOR EXTERNAL USE ONLY

CAUTION POISON

1 FL OZ (30 mL)